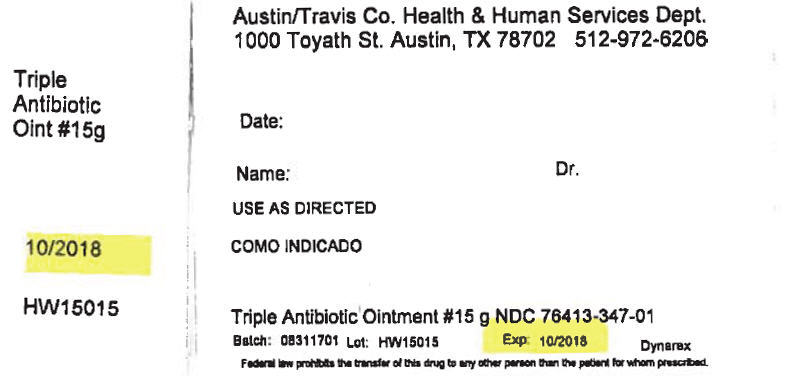 DRUG LABEL: bacitracin zinc, neomycin sulfate and polymyxin b sulfate
NDC: 76413-347 | Form: OINTMENT
Manufacturer: Central Texas Community Health Centers
Category: otc | Type: HUMAN OTC DRUG LABEL
Date: 20170908

ACTIVE INGREDIENTS: BACITRACIN ZINC 400 [iU]/1 g; NEOMYCIN SULFATE 5 mg/1 g; POLYMYXIN B SULFATE 5000 [iU]/1 g
INACTIVE INGREDIENTS: PETROLATUM

Triple Antibiotic Ointment

Active ingredient (in ea. gram) Purpose
Bacitracin Zinc 400 Units First Aid Antibiotic

Neomyxin Sulfate 5mg (Equivalent to 3.5 mg Neomyxin) First Aid Antibiotic

Polymyxin B Sulfate 5000 Units First Aid Antibiotic

Ask a doctor before use:

First aid to help prevent infection in:

- Minor cuts
- scrapes
- burns

Purpose

First aid to help prevent infection in:

- Minor cuts
- scrapes
- burns

Other information

- store at controlled room temperature 15°-30° C (59°-86° F)
- avoid excessive heat and humidity

Inactive ingredients:

Hard Paraffin, Liquid Paraffin, White Soft Paraffin

Keep Out Of Reach Of Children

Warnings

For external use only

Dosage and Administration

- clean the affected areas
- apply a small amount of product (an amount equal to the surface area of the tip of the finger) on the area 1 to 3 times daily
- may be covered with a sterile bandage

Do Not Use:

- if you are allergic to any of the ingredients
- in the eyes
- over large areas of the body
- longer than 1 week unless directed by a doctor

- Stop use and ask a doctor if condition persists or gets worse, or if a rash or other allergic reaction occurs

PRINCIPAL DISPLAY PANEL - 15 g Tube Box Label

Austin/Travis Co. Health & Human Services Dept.
1000 Toyath St. Austin, TX 78702 512-972-6206

Triple
Antibiotic
Oint #15g

Date:

Name:
Dr.

USE AS DIRECTED

10/2018

HW15015

Triple Antibiotic Ointment #15 g NDC 76413-347-01

Batch: 08311701
Lot: HW15015
Exp: 10/2018
Dynarex

Federal law prohibits the transfer of this drug to any other person than the patient for whom prescribed.